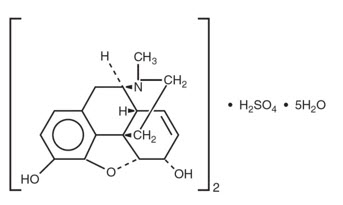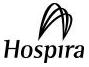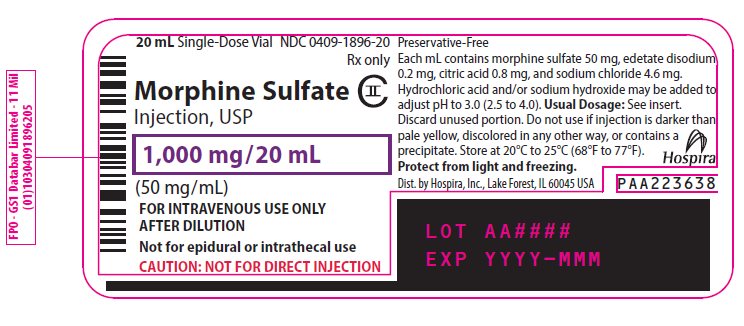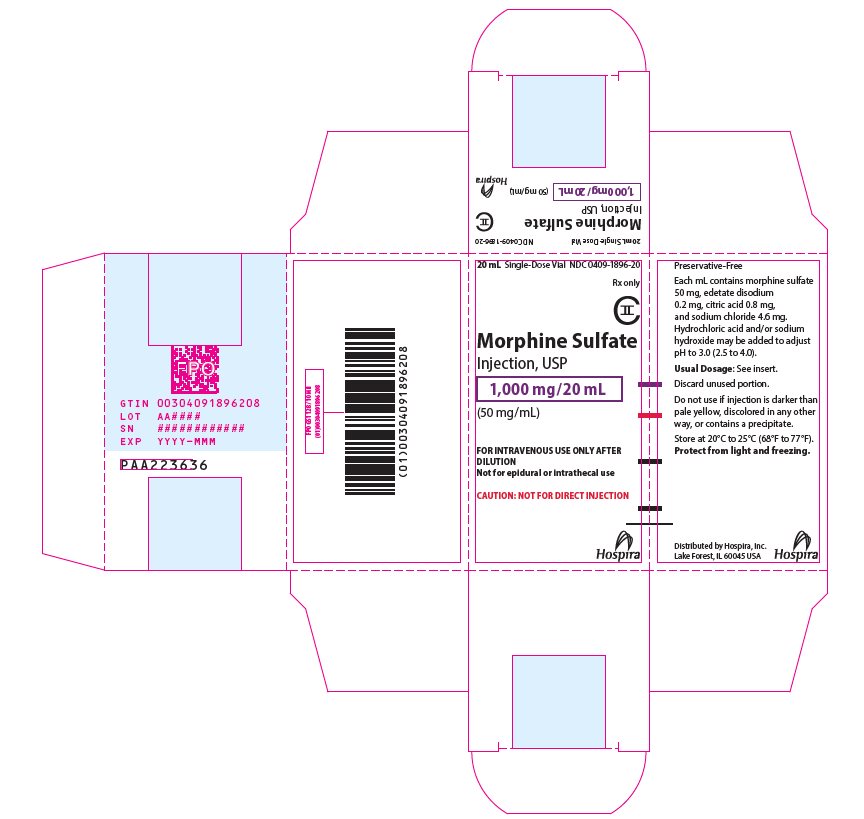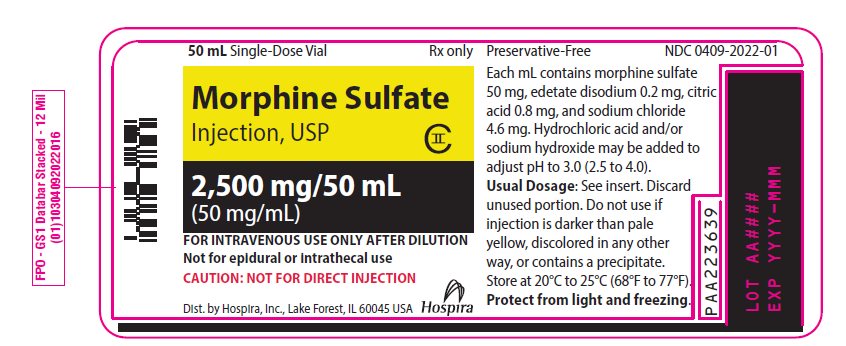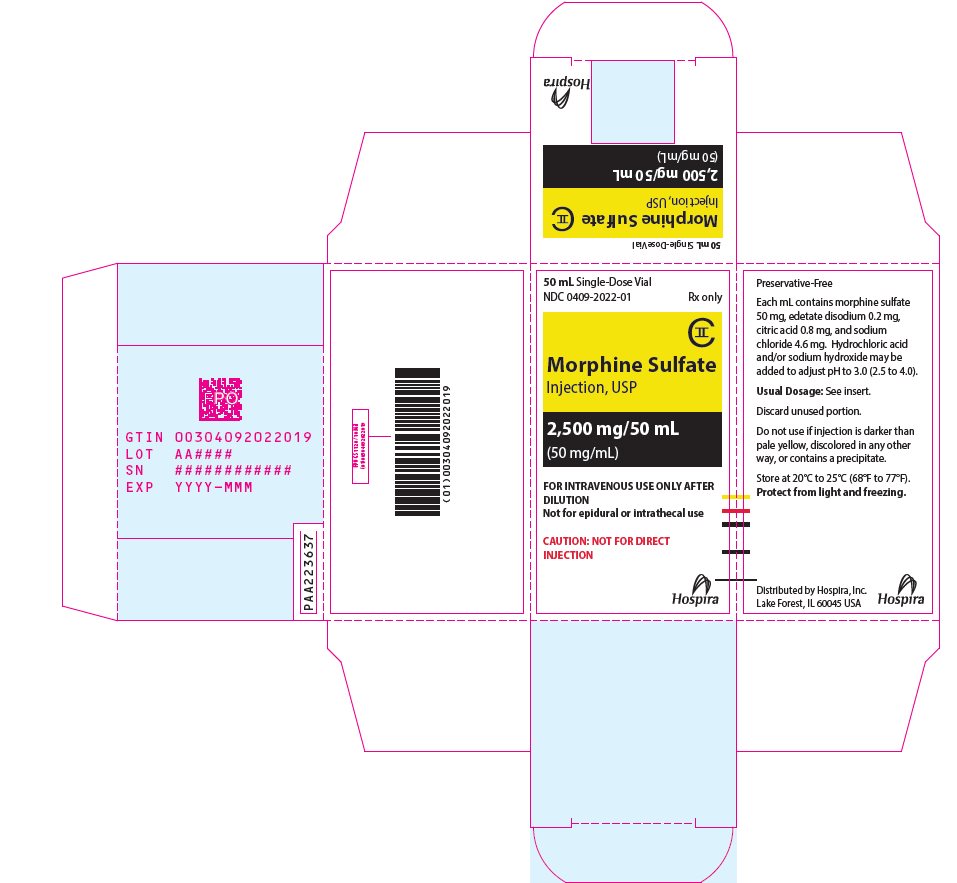 DRUG LABEL: Morphine Sulfate
NDC: 0409-1896 | Form: INJECTION, SOLUTION
Manufacturer: Hospira, Inc.
Category: prescription | Type: HUMAN PRESCRIPTION DRUG LABEL
Date: 20251231
DEA Schedule: CII

ACTIVE INGREDIENTS: MORPHINE SULFATE 50 mg/1 mL
INACTIVE INGREDIENTS: EDETATE DISODIUM 0.2 mg/1 mL; WATER; CITRIC ACID MONOHYDRATE 0.8 mg/1 mL; SODIUM CHLORIDE; HYDROCHLORIC ACID; SODIUM HYDROXIDE

HIGHLIGHTS OF PRESCRIBING INFORMATION

These highlights do not include all the information needed to use MORPHINE SULFATE INJECTION safely and effectively. See full prescribing information for MORPHINE SULFATE INJECTION.
MORPHINE SULFATE INJECTION, for intravenous use, CII
Initial U.S. Approval: 1941

WARNING: SERIOUS AND LIFE-THREATENING RISKS FROM USE OF MORPHINE SULFATE INJECTION

See full prescribing information for complete boxed warning.

- Morphine Sulfate Injection exposes users to risks of addiction, abuse, and misuse, which can lead to overdose and death. Assess patient’s risk before prescribing and reassess regularly for these behaviors and conditions. (5.1)
- Serious, life-threatening, or fatal respiratory depression may occur with use of Morphine Sulfate Injection, especially during initiation or following a dosage increase. To reduce the risk of respiratory depression, proper dosing and titration of ‎Morphine Sulfate Injection are essential. (5.2)
- Concomitant use of opioids with benzodiazepines or other central nervous system (CNS) depressants, including alcohol, may result in profound sedation, respiratory depression, coma, and death. Reserve concomitant prescribing for use in patients for whom alternative treatment options are inadequate. (5.3, 7)
- Advise pregnant women using opioids for an extended period of time of the risk of Neonatal Opioid Withdrawal Syndrome, which may be life-threatening if not recognized and treated. Ensure that management by neonatology expert will be available at delivery. (5.4)

RECENT MAJOR CHANGES

Boxed Warning | 12/2025
Indications and Usage (1) | 12/2025
Dosage and Administration (2.4) | 12/2025
Warnings and Precautions (5.1, 5.2, 5.3, 5.12, 5.14) | 12/2025

1 INDICATIONS AND USAGE

Morphine Sulfate Injection is an opioid agonist indicated in adult and pediatric patients for the management of pain severe enough to require an opioid analgesic and for which alternative treatments are inadequate. (1)
Limitations of Use

Because of the risks of addiction, abuse, misuse, overdose, and death, which can occur at any dosage or duration and persist over the course of therapy, reserve opioid analgesics, including Morphine Sulfate Injection, for use in patients for whom alternative treatment options are ineffective, not tolerated, or would be otherwise inadequate to provide sufficient management of pain. (1, 5.1)

2 DOSAGE AND ADMINISTRATION

- Morphine Sulfate Injection should be prescribed only by healthcare ‎professionals who are knowledgeable about the use of opioids and how ‎to ‎mitigate the associated risks. (2.1)‎
- Use the lowest effective dosage for the shortest duration of time consistent with individual patient treatment goals. Reserve titration to higher ‎doses of Morphine Sulfate Injection for patients in whom lower doses are ‎‎insufficiently effective and in whom the expected benefits of using a ‎higher dose opioid clearly outweigh the substantial risks. (2.1, 5)‎
- Many acute pain conditions (e.g., the pain that occurs with a number ‎of surgical procedures or acute musculoskeletal injuries) require no ‎more ‎than a few days of an opioid analgesic. Clinical guidelines on ‎opioid prescribing for some acute pain conditions are available. (2.1)‎
- Initiate the dosing regimen for each patient ‎individually, taking into account the patient’s underlying cause and ‎severity of ‎pain, prior analgesic treatment and response, and risk ‎factors for addiction, abuse, and misuse. (2.1, 5.1)‎
- Respiratory depression can occur at any time during opioid therapy, ‎especially when initiating and following dosage increases with ‎Morphine ‎Sulfate Injection. Consider this risk when selecting an initial ‎dose and when making dose adjustments. (2.1, 5.2)‎
- Do not inject directly. Morphine Sulfate Injection is intended for continuous intravenous infusion only, after dilution in large volume parenteral solutions. (2.1, 2.5)
- Initial and maintenance dosage in adults: See full prescribing information for recommended dosages in adult patients. (2.2, 2.3)
- Initial and maintenance dosage in pediatric patients: See full prescribing information for recommended dosage in pediatric patients. (2.2, 2.3)
- Periodically reassess patients receiving Morphine Sulfate Injection to evaluate the continued need for opioid analgesics to maintain pain control, for the signs or symptoms of adverse reactions, and for the development of addiction, abuse, or misuse. (2.3)
- Do not rapidly reduce or abruptly discontinue Morphine Sulfate Injection in a physically-dependent patient. (2.4, 5.14)
- See full prescribing information for preparation and storage instructions. (2.5)

3 DOSAGE FORMS AND STRENGTHS

Morphine Sulfate Injection, USP is available in 1,000 mg/20 mL (50 mg/mL) and 2,500 mg/50 mL (50 mg/mL) single-dose flip top vials. (3)

4 CONTRAINDICATIONS

- Significant respiratory depression. (4)
- Acute or severe bronchial asthma in an unmonitored setting or in absence of resuscitative equipment. (4)
- Concurrent use of monoamine oxidase inhibitors (MAOIs) or use of MAOIs within the last 14 days. (4)
- Known or suspected gastrointestinal obstruction, including paralytic ileus. (4)
- Hypersensitivity to morphine. (4)

5 WARNINGS AND PRECAUTIONS

- Cardiovascular Instability: High doses are excitatory. Have naloxone injection and resuscitative equipment immediately available. (5.5)
- Opioid-Induced Hyperalgesia and Allodynia: Opioid-Induced ‎Hyperalgesia (OIH) occurs when an opioid analgesic paradoxically ‎causes an increase in pain, or an increase in sensitivity to pain. If OIH is suspected, carefully consider ‎appropriately decreasing the dose of the current opioid analgesic or ‎opioid rotation. ‎‎(5.6)‎
- Life-Threatening Respiratory Depression in Patients with Chronic Pulmonary Disease or in Elderly, Cachectic, or Debilitated Patients: Monitor closely, particularly during initiation and titration. (5.7)
- Adrenal Insufficiency: If diagnosed, treat with physiologic replacement of corticosteroids, and wean patient off of the opioid. (5.9)
- Severe Hypotension: Monitor during dosage initiation and titration. Avoid use of Morphine Sulfate Injection in patients with circulatory shock. (5.10)
- Risks of Use in Patients with Increased Intracranial Pressure, Brain Tumors, Head Injury, or Impaired Consciousness: Monitor for sedation and respiratory depression. Avoid use of Morphine Sulfate Injection in patients with impaired consciousness or coma. (5.11)

6 ADVERSE REACTIONS

The most serious adverse reactions encountered are respiratory depression, apnea, circulatory depression, respiratory arrest, shock, and cardiac arrest. Other common frequently observed adverse reactions include: sedation, lightheadedness, dizziness, nausea, vomiting, constipation, and diaphoresis. (6)
To report SUSPECTED ADVERSE REACTIONS, contact Pfizer, Inc. at 1-800-438-1985, or FDA at 1-800-FDA-1088 or www.fda.gov/medwatch.

7 DRUG INTERACTIONS

- Serotonergic Drugs: Concomitant use may result in serotonin syndrome. Discontinue Morphine Sulfate Injection if serotonin syndrome is suspected. (7)
- Mixed Agonist/Antagonist and Partial Agonist Opioid Analgesics: Avoid use with Morphine Sulfate Injection because they may reduce analgesic effect of Morphine Sulfate Injection or precipitate withdrawal symptoms. (7)

8 USE IN SPECIFIC POPULATIONS

- Pregnancy: May cause fetal harm. (8.1)
- Geriatric Patients: Use caution during dose selection, starting at the low ‎end of the dosing range while carefully monitoring for side effects. ‎‎(8.5)

FULL PRESCRIBING INFORMATION

WARNING: SERIOUS AND LIFE-THREATENING RISKS FROM USE OF MORPHINE SULFATE INJECTION

Addiction, Abuse, and Misuse

Because the use of Morphine Sulfate Injection exposes patients and other users to the risks of opioid addiction, abuse, and misuse, which can lead to overdose and death, assess each patient's risk prior to prescribing and reassess all patients regularly for the development of these behaviors and conditions [see Warnings and Precautions (5.1)].

Life-Threatening Respiratory Depression

Serious, life-threatening, or fatal respiratory depression may occur with use of Morphine Sulfate Injection, especially during initiation or following a dosage increase. To reduce the risk of respiratory depression, proper dosing and titration of ‎Morphine Sulfate ‎Injection are essential [see Warnings and Precautions (5.2)].

Risks from Concomitant Use with Benzodiazepines or Other CNS Depressants

Concomitant use of opioids with benzodiazepines or other central nervous system (CNS) depressants, including alcohol, may result in profound sedation, respiratory depression, coma, and death. Reserve concomitant prescribing of Morphine Sulfate Injection and benzodiazepines ‎or other CNS depressants for use in patients for whom alternative treatment options are ‎inadequate [see Warnings and Precautions (5.3), Drug Interactions (7)].

Neonatal Opioid Withdrawal Syndrome (NOWS)

Advise pregnant women using opioids for an extended period of time of the risk of Neonatal Opioid Withdrawal Syndrome, which may be life-threatening if not recognized and treated. Ensure that management by neonatology expert will be available at delivery [see Warnings and Precautions (5.4)].

1 INDICATIONS AND USAGE

Morphine Sulfate Injection is indicated in adult and pediatric patients for the management of pain severe enough to require an opioid analgesic and for which alternative treatments are inadequate.

Limitations of Use:

Because of the risks of addiction, abuse, misuse, overdose, and death, which can occur at any dosage or duration and persist over the course of therapy [see Warnings and Precautions (5.1)], reserve opioid analgesics, including Morphine Sulfate Injection, for use in patients for whom alternative treatment options are ineffective, not tolerated, or would be otherwise inadequate to provide sufficient management of pain.

2 DOSAGE AND ADMINISTRATION

2.1 Important Dosage and Administration Instructions

- Morphine Sulfate Injection is for intravenous use only. It is not for intrathecal or epidural use.
- Do not inject directly. Morphine Sulfate Injection is intended for continuous intravenous infusion only, after dilution in large volume parenteral solutions [see Dosage and Administration (2.5)].
- Dosing errors can result in accidental overdose and death. Avoid dosing errors that may result from confusion between mg and mL and confusion with morphine injections of different concentrations when prescribing, dispensing, and administering Morphine Sulfate Injection. Ensure that the dose is communicated and dispensed accurately.
- Morphine Sulfate Injection should be prescribed only by healthcare ‎professionals who are ‎knowledgeable about the use of opioids and how ‎to mitigate the associated risks.‎
- Use the lowest effective dosage for the shortest duration of time consistent with individual patient treatment goals [see Warnings and Precautions (5)]. Because the risk of overdose increases as opioid doses ‎increase, reserve titration to higher doses of ‎Morphine Sulfate Injection for ‎patients in whom lower doses are insufficiently effective and in whom ‎the ‎expected benefits of using a higher dose opioid clearly outweigh the ‎substantial risks.‎
- Many acute pain conditions (e.g., the pain that occurs with a number ‎of surgical procedures or acute ‎musculoskeletal injuries) require no ‎more than a few days of an opioid analgesic. Clinical guidelines on ‎‎opioid prescribing for some acute pain conditions are available.‎
- There is variability in the opioid analgesic dose and duration needed to ‎adequately manage pain due ‎both to the cause of pain and to ‎individual patient factors. ‎Initiate the dosing regimen for each patient individually, taking into account the patient's underlying cause and severity of pain, prior analgesic treatment and response, and risk factors for addiction, abuse, and misuse [see Warnings and Precautions (5.1)].
- Respiratory depression can occur at any time during opioid therapy, especially when initiating and following dosage increases with Morphine Sulfate Injection. Consider this risk when selecting an initial dose and when making dose adjustments [see Warnings and Precautions (5.2)].
- Morphine must be injected slowly; rapid intravenous administration may result in chest wall rigidity.
- Inspect Morphine Sulfate Injection for particulate matter and discoloration prior to administration. Do not use if color is darker than pale yellow, if it is discolored in any other way, or if it contains a precipitate.

2.2 Initial Dosage

Continuous Intravenous Infusion

Use the lowest dose necessary to achieve adequate analgesia.‎

Adults

Adults: Initiate treatment in a dosing range of 0.02 mg/kg/hour to 0.1 mg/kg/hour as needed. The dosage should be titrated according to the patient's response [see Dosage and Administration (2.3)].

For opioid-naïve patients, a maximum dosing rate should not exceed 10 mg/hour.

For opioid-tolerant patients, including patients who, because of their condition, have a high analgesic requirement (e.g., terminal cancer pain), dosing rates as high as 30 mg/hour or higher may be required to manage pain.

Pediatric patients

Patients 1 to less than 17 years old:

Initiate intravenous infusion in patients 1 to less than 17 years old as follows:

- Less than 50 kg body weight: 20 mcg/kg/hour to 30 mcg/kg/hour (0.02 mg/kg/hour to 0.03 mg/kg/hour)
- Greater than or equal to 50 kg body weight: 1,500 mcg/hour (1.5 mg/hour)

Patients less than 1 year old, including neonates:

- Initiate treatment in a dosing range of 0.005 mg/kg/hour to 0.01 mg/kg/hour.
- Cardiorespiratory function should be monitored in patients less than 3 months of age. The infusion rate should be adjusted based on clinical signs of inadequate pain relief and/or increased somnolence.
- For premature infants and former premature infants with chronic lung disease and up to 5 to 6 months of age, careful monitoring for depressed hypoxic drive is required following opioid administration.

The dosage should be titrated according to the patient's response [see Dosage and Administration (2.3)]. For opioid-tolerant patients, including patients with a high analgesic requirement (e.g., terminal cancer pain, sickle-cell disease crisis), higher initial doses may be required.

2.3 Titration and Maintenance of Therapy

Titrate the dose based upon the individual patient’s response to their initial dose ‎of Morphine Sulfate ‎Injection.‎ Individually titrate Morphine Sulfate Injection to a dosage that provides adequate analgesia and minimizes adverse reactions. Continually reevaluate patients receiving Morphine Sulfate Injection to assess the maintenance of pain control, signs and symptoms of opioid withdrawal, and other adverse reactions, as well to reassess for the development of addiction, abuse, or misuse [see Warnings and Precautions (5.1, 5.14)]. If after increasing the dosage, unacceptable opioid‑related adverse reactions are observed, ‎(including an increase in pain after dosage increase)‎,‎ consider reducing the dosage ‎[see Warnings and Precautions (5)]‎. Adjust the dosage to obtain an appropriate balance between management of pain and opioid-related adverse reactions.

Pediatric patients

Patients 1 to less than 17 years old:

Recommended maintenance dosage for patients 1 to less than 17 years old is as follows:

- Less than 60 kg body weight: 10 mcg/kg/hour to 60 mcg/kg/hour (0.01 mg/kg/hour to 0.06 mg/kg/hour)
- Greater than or equal to 60 kg body weight: 0.8 mg/hour to 3 mg/hour

The maintenance dosage in pediatric patients should be adjusted based on individual patient's needs to obtain an appropriate balance between effective pain management and opioid-related adverse reactions.

2.4 Safe Reduction and Discontinuation of Morphine Sulfate Injection

When a patient who has been taking Morphine Sulfate Injection regularly and may be physically dependent no longer requires therapy with Morphine Sulfate Injection, taper the dose gradually, by 25% to 50% every 2 to 4 days, while monitoring carefully for signs and symptoms of withdrawal. If the patient develops these signs or symptoms, raise the dose to the previous level and taper more slowly, either by increasing the interval between decreases, decreasing the amount of change in dose, or both. Do not rapidly reduce or abruptly discontinue Morphine Sulfate Injection in patients who may be physically dependent on opioids [see Warnings and Precautions (5.14), Drug Abuse and Dependence (9.3)].

2.5 Preparation of Solutions for Infusion

Morphine Sulfate Injection is incompatible with admixtures of soluble barbiturates, chlorothiazide, aminophylline, heparin, meperidine, methicillin, phenytoin, sodium bicarbonate, iodide, sulfadiazine and sulfisoxazole.

Single-dose Flip Top Vial

Morphine Sulfate Injection USP, 1,000 mg/20 mL (50 mg/mL), and 2,500 mg/50 mL (50 mg/mL) single-dose vials are for the preparation of large volume parenteral solutions and are not for direct injection.

Dilute Morphine Sulfate Injection in either Dextrose 5% injection or Sodium Chloride 0.9% injection to a final concentration of 0.1 mg/mL to 5 mg/mL, as determined by the patient's needs, prior to administration (see Table 1 for instructions regarding dilution). Preparations in Sodium Chloride 0.9% injection are stable for 14 days at room temperature [20°C to 25°C (68°F to 77°F)] or under refrigerated conditions [2°C to 8°C (36°F to 46°F)]. Preparations in Dextrose 5% injection are stable for up to 72 hours at room temperature [20°C to 25°C (68°F to 77°F)] or for 14 days under refrigerated conditions [2°C to 8°C (36°F to 46°F)].

Table 1: Examples of Infusion Preparation
Concentration | Diluent | Final Concentration Morphine Sulfate
Morphine 50 mg/mL | 5% Dextrose or 0.9% NaCl
20 mL vial | 980 mL | 1 mg/mL
50 mL vial | 950 mL | 2.5 mg/mL

3 DOSAGE FORMS AND STRENGTHS

Morphine Sulfate Injection, USP is available as single-dose flip top vials for the preparation of large volume parenteral solutions in the following presentations:

- 1,000 mg/20 mL (50 mg/mL) clear and colorless to pale yellow solution, and
- 2,500 mg/50 mL (50 mg/mL) clear and colorless to pale yellow solution

4 CONTRAINDICATIONS

Morphine Sulfate Injection is contraindicated in patients with:

- Significant respiratory depression [see Warnings and Precautions (5.2)]
- Acute or severe bronchial asthma in an unmonitored setting or in the absence of resuscitative equipment [see Warnings and Precautions (5.7)]
- Concurrent use of monoamine oxidase inhibitors (MAOIs) or use of MAOIs within the last 14 days [see Warnings and Precautions (5.8)]
- Known or suspected gastrointestinal obstruction, including paralytic ileus [see Warnings and Precautions (5.12)]
- Hypersensitivity to morphine (e.g., anaphylaxis) [see Adverse Reactions (6)]

5 WARNINGS AND PRECAUTIONS

5.1 Addiction, Abuse, and Misuse

Morphine Sulfate Injection contains morphine, a Schedule II controlled substance. As an opioid, Morphine Sulfate Injection exposes users to the risks of addiction, abuse, and misuse [see Drug Abuse and Dependence (9)].

Although the risk of addiction in any individual is unknown, it can occur in patients appropriately prescribed Morphine Sulfate Injection. Addiction can occur at recommended dosages and if the drug is misused or abused. The risk of opioid-related overdose or overdose-related death is increased with higher opioid doses, and this risk persists over the course of therapy. In postmarketing studies, addiction, abuse, misuse, and fatal and non-fatal opioid overdose were observed in patients with long-term opioid use [see Adverse Reactions (6)].

Assess each patient's risk for opioid addiction, abuse, or misuse prior to prescribing Morphine Sulfate Injection, and monitor all patients receiving morphine sulfate for the development of these behaviors and conditions. Risks are increased in patients with a personal or family history of substance abuse (including drug or alcohol abuse or addiction) or mental illness (e.g., major depression). The potential for these risks should not, however, prevent the proper management of pain in any given patient. Patients at increased risk may be prescribed opioids such as Morphine Sulfate Injection but use in such patients necessitates intensive counseling about the risks and proper use of Morphine Sulfate Injection along with intensive monitoring for signs of addiction, abuse, and misuse.

Opioids are sought for nonmedical use and are subject to diversion from ‎legitimate prescribed use. Consider these risks when prescribing or dispensing Morphine Sulfate Injection. Strategies to reduce these risks include prescribing the drug in the smallest appropriate quantity. Contact local state professional licensing board or state-controlled substances authority for information on how to prevent and detect abuse or diversion of this product.

5.2 Life-Threatening Respiratory Depression

Serious, life-threatening, or fatal respiratory depression has been reported with the use of opioids, even when used as recommended. Respiratory depression, if not immediately recognized and treated, may lead to respiratory arrest and death. Management of respiratory depression may include close observation, supportive measures, and use of opioid overdose reversal agents (e.g., naloxone, nalmefene), depending on the patient's clinical status [see Overdosage (10)]. Carbon dioxide (CO2) retention from opioid-induced respiratory depression can exacerbate the sedating effects of opioids.

While serious, life-threatening, or fatal respiratory depression can occur at any time during the use of Morphine Sulfate Injection, the risk is greatest during the initiation of therapy or following a dosage increase. Because of a delay in the maximum CNS effect with intravenously administered Morphine Sulfate Injection (30 min), rapid administration may result in overdosing. The respiratory depression may be severe and could require intervention [see Overdosage (10)].

To reduce the risk of respiratory depression, proper dosing and titration of Morphine Sulfate Injection are essential [see Dosage and Administration (2.3)]. Overestimating the Morphine Sulfate Injection dosage when converting patients from another opioid product can result in a fatal overdose with the first dose.

Opioids can cause sleep-related breathing disorders including central sleep apnea (CSA) and sleep-related hypoxemia. Opioid use increases the risk of CSA in a dose-dependent fashion. In patients who present with CSA, consider decreasing the opioid dosage using best practices for opioid taper [see Dosage and Administration (2.3)].

5.3 Risks from Concomitant Use with Benzodiazepines or Other Central Nervous System Depressants

Profound sedation, respiratory depression, coma, and death may result from the concomitant use of Morphine Sulfate Injection with benzodiazepines and/or other CNS depressants, including alcohol (e.g., non-benzodiazepine sedatives/hypnotics, anxiolytics, tranquilizers, muscle relaxants, general anesthetics, antipsychotics, gabapentinoids [gabapentin or pregabalin], and other opioids). Because of these risks, reserve concomitant prescribing of these drugs for use in patients for whom alternative treatment options are inadequate.

Observational studies have demonstrated that concomitant use of opioid analgesics and benzodiazepines increases the risk of drug-related mortality compared to use of opioid analgesics alone. Because of similar pharmacological properties, it is reasonable to expect similar risk with the concomitant use of other CNS depressant drugs with opioid analgesics [see Drug Interactions (7)].

If the decision is made to prescribe a benzodiazepine or other CNS depressant concomitantly with an opioid analgesic, prescribe the lowest effective dosages and minimum durations of concomitant use. In patients already receiving an opioid analgesic, prescribe a lower initial dose of the benzodiazepine or other CNS depressant than indicated in the absence of an opioid, and titrate based on clinical response. If an opioid analgesic is initiated in a patient already taking a benzodiazepine or other CNS depressant, prescribe a lower initial dose of the opioid analgesic, and titrate based on clinical response. Monitor patients closely for signs and symptoms of respiratory depression and sedation.

Advise both patients and caregivers about the risks of respiratory depression and sedation when Morphine Sulfate Injection is used with benzodiazepines or other CNS depressants (including alcohol and illicit drugs). Advise patients not to drive or operate heavy machinery until the effects of concomitant use of the benzodiazepine or other CNS depressant have been determined. Screen patients for risk of substance use disorders, including opioid abuse and misuse, and warn them of the risk for overdose and death associated with the use of additional CNS depressants including alcohol and illicit drugs [see Drug Interactions (7)].

5.4 Neonatal Opioid Withdrawal Syndrome

Use of Morphine Sulfate Injection for an extended period of time during pregnancy can result in withdrawal in the neonate. Neonatal opioid withdrawal syndrome, unlike opioid withdrawal syndrome in adults, may be life-threatening if not recognized and treated, and requires management according to protocols developed by neonatology experts. Observe newborns for signs of neonatal opioid withdrawal syndrome and manage accordingly. Advise pregnant women using opioids for an extended period of time of the risk of neonatal opioid withdrawal syndrome and ensure that management by neonatology experts will be available at delivery [see Use in Specific Populations (8.1)].

5.5 Cardiovascular Instability

While low doses of intravenously administered morphine have little effect on cardiovascular stability, high doses are excitatory, resulting from sympathetic hyperactivity and increase in circulatory catecholamines. Have naloxone injection and resuscitative equipment immediately available for use in case of life-threatening or intolerable side effects and whenever morphine therapy is being initiated.

5.6 Opioid-Induced Hyperalgesia and Allodynia

Opioid-Induced Hyperalgesia (OIH) occurs when an opioid analgesic ‎paradoxically causes an increase in ‎pain, or an increase in sensitivity to pain. ‎This condition differs from tolerance, which is the need for ‎increasing doses of ‎opioids to maintain a defined effect [see Drug Abuse and Dependence (9.3)]. Symptoms of OIH ‎‎include (but may not be limited to) increased levels of pain upon opioid dosage ‎increase, decreased ‎levels of pain upon opioid dosage decrease, or pain from ‎ordinarily non-painful stimuli (allodynia). ‎These symptoms may suggest OIH only ‎if there is no evidence of underlying disease progression, opioid ‎tolerance, ‎opioid withdrawal, or addictive behavior.‎

Cases of OIH have been reported, both with short-term and longer-term use of ‎opioid analgesics. Though the mechanism of OIH is not fully understood, ‎multiple biochemical pathways have been implicated. Medical literature suggests ‎a strong biologic plausibility between opioid analgesics and OIH and allodynia. If ‎a patient is suspected to be experiencing OIH, carefully consider appropriately ‎decreasing the dose of the current opioid analgesic or opioid rotation (safely ‎switching the patient to a different opioid moiety) [see Dosage and ‎Administration (2.4), Warnings and Precautions (5.14)].‎

5.7 Life-Threatening Respiratory Depression in Patients with Chronic Pulmonary Disease or in Elderly, Cachectic, or Debilitated Patients

The use of Morphine Sulfate Injection in patients with acute or severe bronchial asthma in an unmonitored setting or in the absence of resuscitative equipment is contraindicated.

Patients with Chronic Pulmonary Disease: Morphine Sulfate Injection-treated patients with significant chronic obstructive pulmonary disease or cor pulmonale, and those with a substantially decreased respiratory reserve, hypoxia, hypercapnia, or pre-existing respiratory depression are at increased risk of decreased respiratory drive including apnea, even at recommended dosages of Morphine Sulfate Injection [see Warnings and Precautions (5.2)].

Elderly, Cachectic, or Debilitated Patients: Life-threatening respiratory depression is more likely to occur in elderly, cachectic, or debilitated patients because they may have altered pharmacokinetics or altered clearance compared to younger, healthier patients [see Warnings and Precautions (5.2)].

Monitor such patients closely, particularly when initiating and titrating Morphine Sulfate Injection and when Morphine Sulfate Injection is given concomitantly with other drugs that depress respiration [see Warnings and Precautions (5.2)]. Alternatively, consider the use of non-opioid analgesics in these patients.

5.8 Interaction with Monoamine Oxidase Inhibitors

Monoamine oxidase inhibitors (MAOIs) may potentiate the effects of morphine, including respiratory depression, coma, and confusion. Morphine Sulfate Injection should not be used in patients taking MAOIs or within 14 days of stopping such treatment.

5.9 Adrenal Insufficiency

Cases of adrenal insufficiency have been reported with opioid use, more often following greater than one month of use. Presentation of adrenal insufficiency may include non-specific symptoms and signs including nausea, vomiting, anorexia, fatigue, weakness, dizziness, and low blood pressure. If adrenal insufficiency is suspected, confirm the diagnosis with diagnostic testing as soon as possible. If adrenal insufficiency is diagnosed, treat with physiologic replacement doses of corticosteroids. Wean the patient off of the opioid to allow adrenal function to recover and continue corticosteroid treatment until adrenal function recovers. Other opioids may be tried as some cases reported use of a different opioid without recurrence of adrenal insufficiency. The information available does not identify any particular opioids as being more likely to be associated with adrenal insufficiency.

5.10 Severe Hypotension

Morphine Sulfate Injection may cause severe hypotension including orthostatic hypotension and syncope in ambulatory patients. There is increased risk in patients whose ability to maintain blood pressure has already been compromised by a reduced blood volume or concurrent administration of certain CNS depressant drugs (e.g., phenothiazines or general anesthetics) [see Drug Interactions (7)]. Monitor these patients for signs of hypotension after initiating or titrating the dosage of Morphine Sulfate Injection. In patients with circulatory shock, Morphine Sulfate Injection may cause vasodilation that can further reduce cardiac output and blood pressure. Avoid the use of Morphine Sulfate Injection in patients with circulatory shock.

5.11 Risks of Use in Patients with Increased Intracranial Pressure, Brain Tumors, Head Injury, or Impaired Consciousness

In patients who may be susceptible to the intracranial effects of CO2 retention (e.g., those with evidence of increased intracranial pressure or brain tumors), Morphine Sulfate Injection may reduce respiratory drive, and the resultant CO2 retention can further increase intracranial pressure. Monitor such patients for worsening of signs of increasing intracranial pressure.‎ Monitor patients for signs of sedation and respiratory depression, particularly when initiating therapy with Morphine Sulfate Injection.

Opioids may also obscure the clinical course in a patient with a head injury. Avoid the use of Morphine Sulfate Injection in patients with impaired consciousness or coma.

5.12 Risks of Gastrointestinal Complications

Morphine Sulfate Injection is contraindicated in patients with known or suspected gastrointestinal obstruction, including paralytic ileus.

The morphine in Morphine Sulfate Injection may cause spasm of the sphincter of Oddi. Opioids may cause increases in serum amylase. Monitor patients with biliary tract disease, including acute pancreatitis, for worsening symptoms.

Cases of opioid-induced esophageal dysfunction (OIED) have been reported in patients taking opioids. The risk of OIED may increase as the dose and/or duration of opioids increases. Regularly evaluate patients for signs and symptoms of OIED (e.g., dysphagia, regurgitation, non-cardiac chest pain) and, if necessary, adjust opioid therapy as clinically appropriate [see Clinical Pharmacology (12.2)].

5.13 Increased Risk of Seizures in Patients with Seizure Disorders

The morphine in Morphine Sulfate Injection may increase the frequency of seizures in patients with seizure disorders, and may increase the risk of seizures occurring in other clinical settings associated with seizures. Monitor patients with a history of seizure disorders for worsened seizure control during Morphine Sulfate Injection therapy.

Excitation of the central nervous system, resulting in convulsions, may accompany high doses of morphine given intravenously.

5.14 Withdrawal

Avoid the use of mixed agonist/antagonist (e.g, pentazocine, nalbuphine, and butorphanol) or partial agonist (e.g., buprenorphine) analgesics in patients who are receiving a full opioid agonist analgesic, including Morphine Sulfate Injection. In these patients, mixed agonist/antagonist and partial agonist analgesics may reduce the analgesic effect and/or precipitate withdrawal symptoms [see Drug Interactions (7)].

When discontinuing Morphine Sulfate Injection in a physically-dependent patient, gradually taper the dosage [see Dosage and Administration (2.4)]. Do not rapidly reduce or abruptly discontinue Morphine Sulfate Injection in these patients [see Drug Abuse and Dependence (9.3)].

5.15 Risks of Driving and Operating Machinery

Morphine Sulfate Injection may impair the mental or physical abilities needed to perform potentially hazardous activities such as driving a car or operating machinery. Warn patients not to drive or operate dangerous machinery unless they are tolerant to the effects of Morphine Sulfate Injection and know how they will react to the medication.

6 ADVERSE REACTIONS

The following serious adverse reactions are described, or described in greater detail, in other sections:

- Addiction, Abuse, and Misuse [see Warnings and Precautions (5.1)]
- Life-Threatening Respiratory Depression [see Warnings and Precautions (5.2)]
- Interactions with Benzodiazepines or Other CNS Depressants [see Warnings and Precautions (5.3)]
- Neonatal Opioid Withdrawal Syndrome [see Warnings and Precautions (5.4)]
- Cardiovascular Instability [see Warnings and Precautions (5.5)]
- Opioid-Induced Hyperalgesia and Allodynia [see Warnings and Precautions (5.6)]
- Adrenal Insufficiency [see Warnings and Precautions (5.9)]
- Severe Hypotension [see Warnings and Precautions (5.10)]
- Gastrointestinal Adverse Reactions [see Warnings and Precautions (5.12)]
- Seizures [see Warnings and Precautions (5.13)]
- Withdrawal [see Warnings and Precautions (5.14)]

The following adverse reactions associated with the use of morphine were identified in clinical studies or postmarketing reports. Because some of these reactions were reported voluntarily from a population of uncertain size, it is not always possible to reliably estimate their frequency or establish a causal relationship to drug exposure.

Serious adverse reactions associated with Morphine Sulfate Injection included respiratory depression, apnea, and to a lesser degree, circulatory depression, respiratory arrest, shock, and cardiac arrest. Rarely, anaphylactoid reactions have been reported when morphine or other phenanthrene alkaloids of opium are administered intravenously.

The most frequently observed adverse reactions included sedation, lightheadedness, dizziness, nausea, vomiting, constipation, and diaphoresis.

Other possible adverse reactions included:

Central Nervous System – Euphoria, dysphoria, weakness, headache, agitation, tremor, uncoordinated muscle movements, visual disturbances, transient hallucinations and disorientation.

Gastrointestinal – Constipation, biliary tract spasm.

Cardiovascular – Tachycardia, bradycardia, palpitation, faintness, syncope, and orthostatic hypotension.

Genitourinary – Oliguria and urinary retention; an antidiuretic effect has been reported.

Allergic – Pruritus, urticaria, and skin rashes. Anaphylactoid reactions have been reported following intravenous administration.

Other – Opioid-induced histamine release may be responsible for the flushing of the face, diaphoresis, and pruritus often seen with these drugs. Wheals and urticaria at the site of injection are probably related to histamine release. Local tissue irritation, pain and induration have been reported following repeated subcutaneous injection. Morphine may alter temperature regulation in susceptible individuals and will depress the cough reflex.

Serotonin syndrome: Cases of serotonin syndrome, a potentially life-threatening condition, have been reported during concomitant use of opioids with serotonergic drugs.

Adrenal insufficiency: Cases of adrenal insufficiency have been reported with opioid use, more often following greater than one month of use.

Anaphylaxis: Anaphylaxis has been reported with ingredients contained in Morphine Sulfate Injection.

Androgen deficiency: Cases of androgen deficiency have occurred with use of opioids for an extended period of time [see Clinical Pharmacology (12.2)].

Hyperalgesia and Allodynia: Cases of hyperalgesia and allodynia have been ‎reported with opioid therapy ‎of any duration [see Warnings and Precautions ‎‎(5.6)]‎.‎

Hypoglycemia: Cases of hypoglycemia have been reported in patients ‎taking opioids. Most reports were in ‎patients with at least one ‎predisposing risk factor (e.g., diabetes).‎

Opioid-induced esophageal dysfunction (OIED): Cases of OIED have been reported in patients taking opioids and may occur more frequently in patients taking higher doses of opioids, and/or in patients taking opioids longer term [see Warnings and Precautions (5.12)].

Adverse Reactions from Observational Studies

A prospective, observational cohort study estimated the risks of addiction, abuse, and misuse in patients initiating long-term use of Schedule II opioid analgesics between 2017 and 2021. Study participants included in one or more analyses had been enrolled in selected insurance plans or health systems for at least one year, were free of at least one outcome at baseline, completed a minimum number of follow-up assessments, and either: 1) filled multiple extended-release/long-acting opioid analgesic prescriptions during a 90-day period (n=978); or 2) filled any Schedule II opioid analgesic prescriptions covering at least 70 of 90 days (n=1,244). Those included also had no dispensing of the qualifying opioids in the previous 6 months.

Over 12 months:

- approximately 1% to 6% of participants across the two cohorts newly met criteria for addiction, as assessed with two validated interview-based measures of moderate-to-severe opioid use disorder based on Diagnostic and Statistical Manual of Mental Disorders, Fifth Edition (DSM-5) criteria, and
- approximately 9% and 22% of participants across the two cohorts newly met criteria for prescription opioid abuse and misuse [defined in Drug Abuse and Dependence (9.2)], respectively, as measured with a validated self-reported instrument.

A retrospective, observational cohort study estimated the risk of opioid-involved overdose or opioid overdose-related death in patients with new long-term use of Schedule II opioid analgesics from 2006 through 2016 (n=220,249). Included patients had been enrolled in either one of two commercial insurance programs, one managed care program, or one Medicaid program for at least 9 months. New long-term use was defined as having Schedule II opioid analgesic prescriptions covering at least 70 days’ supply over the 3 months prior to study entry and none during the preceding 6 months. Patients were excluded if they had an opioid-involved overdose in the 9 months prior to study entry. Overdose was measured using a validated medical code-based algorithm with linkage to the National Death Index database. The 5-year cumulative incidence estimates for opioid-involved overdose or opioid overdose-related death ranged from approximately 1.5% to 4% across study sites, counting only the first event during follow-up. Approximately 17% of first opioid overdoses observed over the entire study period (5-11 years, depending on the study site) were fatal. Higher baseline opioid dose was the strongest and most consistent predictor of opioid-involved overdose or opioid overdose-related death. Study exclusion criteria may have selected patients at lower risk of overdose, and substantial loss to follow-up (approximately 80%) also may have biased estimates.

The risk estimates from the studies described above may not be generalizable to all patients receiving opioid analgesics, such as those with exposures shorter or longer than the duration evaluated in the studies.

7 DRUG INTERACTIONS

Table 2 includes clinically significant drug interactions with Morphine Sulfate Injection.

Table 2: Clinically Significant Drug Interactions with Morphine Sulfate Injection
Benzodiazepines and Other Central Nervous System (CNS) Depressants
Clinical Impact: | Due to additive pharmacologic effect, the concomitant use of benzodiazepines or other CNS depressants, including alcohol, can increase the risk of hypotension, respiratory depression, profound sedation, coma, and death [see Warnings and Precautions (5.3)].
Intervention: | Reserve concomitant prescribing of these drugs for use in patients for whom alternative treatment options are inadequate. Limit dosages and durations to the minimum required. Monitor patients closely for signs of respiratory depression and sedation.
Examples: | Benzodiazepines and other sedatives/hypnotics, anxiolytics, tranquilizers, muscle relaxants, general anesthetics, antipsychotics, gabapentinoids (gabapentin or pregabalin), other opioids, alcohol.
Serotonergic Drugs
Clinical Impact: | The concomitant use of opioids with other drugs that affect the serotonergic neurotransmitter system has resulted in serotonin syndrome.
Intervention: | If concomitant use is warranted, carefully observe the patient, particularly during treatment initiation and dose adjustment. Discontinue Morphine Sulfate Injection if serotonin syndrome is suspected.
Examples: | Selective serotonin reuptake inhibitors (SSRIs), serotonin and norepinephrine reuptake inhibitors (SNRIs), tricyclic antidepressants (TCAs), triptans, 5-HT3 receptor antagonists, drugs that affect the serotonin neurotransmitter system (e.g., mirtazapine, trazodone, tramadol), certain muscle relaxants (i.e., cyclobenzaprine, metaxalone), monoamine oxidase (MAO) inhibitors (those intended to treat psychiatric disorders and also others, such as linezolid and intravenous methylene blue).
Monoamine Oxidase Inhibitors (MAOIs)
Clinical Impact: | MAOI interactions with opioids may manifest as serotonin syndrome or opioid toxicity (e.g., respiratory depression, coma) [see Warnings and Precautions (5.2, 5.8)].
Intervention: | Do not use Morphine Sulfate Injection in patients taking MAOIs or within 14 days of stopping such treatment.; If urgent use of an opioid is necessary, use test doses and frequent titration of small doses of other opioids (such as oxycodone, oxymorphone, hydrocodone, or buprenorphine) to treat pain while closely monitoring blood pressure and signs and symptoms of CNS and respiratory depression.
Examples: | phenelzine, tranylcypromine, linezolid
Mixed Agonist/Antagonist and Partial Agonist Opioid Analgesics
Clinical Impact: | May reduce the analgesic effect of Morphine Sulfate Injection and/or precipitate withdrawal symptoms.
Intervention: | Avoid concomitant use.
Examples: | butorphanol, nalbuphine, pentazocine, buprenorphine
Muscle Relaxants
Clinical Impact: | Morphine may enhance the neuromuscular blocking action of skeletal muscle relaxants and produce an increased degree of respiratory depression.
Intervention: | Monitor patients for signs of respiratory depression that may be greater than otherwise expected and decrease the dosage of Morphine Sulfate Injection and/or the muscle relaxant as necessary.
Examples: | Cyclobenzaprine, metaxalone.
Cimetidine
Clinical Impact: | Concomitant administration of Morphine Sulfate Injection and cimetidine has been reported to precipitate apnea, confusion, and muscle twitching in an isolated report.
Intervention: | Monitor patients for increased respiratory and CNS depression when receiving cimetidine concomitantly with Morphine Sulfate Injection.
Diuretics
Clinical Impact: | Opioids can reduce the efficacy of diuretics by inducing the release of antidiuretic hormone.
Intervention: | Monitor patients for signs of diminished diuresis and/or effects on blood pressure and increase the dosage of the diuretic as needed.
Anticholinergic Drugs
Clinical Impact: | The concomitant use of anticholinergic drugs may increase risk of urinary retention and/or severe constipation, which may lead to paralytic ileus.
Intervention: | Monitor patients for signs of urinary retention or reduced gastric motility when Morphine Sulfate Injection is used concomitantly with anticholinergic drugs.
Oral P2Y12 Inhibitors
Clinical Impact: | The co-administration of oral P2Y12 inhibitors and intravenous morphine sulfate can decrease the absorption and peak concentration of oral P2Y12 inhibitors and delay the onset of the antiplatelet effect.
Intervention: | Consider the use of a parenteral antiplatelet agent in the setting of acute coronary syndrome requiring co-administration of intravenous morphine sulfate.
Examples: | clopidogrel, prasugrel, ticagrelor

8 USE IN SPECIFIC POPULATIONS

8.1 Pregnancy

Risk Summary

Use of opioid analgesics for an extended period of time during pregnancy can cause neonatal opioid withdrawal syndrome [see Warnings and Precautions (5.4)]. There are no available data with Morphine Sulfate Injection in pregnant women to inform a drug-associated risk for major birth defects and miscarriage or adverse maternal outcomes‎.‎ There are adverse outcomes reported with fetal exposure to opioid analgesics [see Clinical ‎‎Considerations]‎. Published studies with morphine use during pregnancy have not reported a clear association with morphine and major birth defects [see Human Data]. In published animal reproduction studies, morphine administered subcutaneously during the early gestational period produced neural tube defects (i.e., exencephaly and cranioschisis) at 5 and 16 times the human daily dose of 60 mg based on body surface area (HDD) in hamsters and mice, respectively, lower fetal body weight and increased incidence of abortion at 0.4 times the HDD in the rabbit, growth retardation at 6 times the HDD in the rat, and axial skeletal fusion and cryptorchidism at 16 times the HDD in the mouse. Administration of morphine sulfate to pregnant rats during organogenesis and through lactation resulted in cyanosis, hypothermia, decreased brain weights, pup mortality, decreased pup body weights, and adverse effects on reproductive tissues at 3–4 times the HDD; and long-term neurochemical changes in the brain of offspring which correlate with altered behavioral responses that persist through adulthood at exposures comparable to and less than the HDD [see Animal Data]. Based on animal data, advise pregnant women of the potential risk to a fetus.

The background risk of major birth defects and miscarriage for the indicated population is unknown. All pregnancies have a background risk of birth defect, loss, or other adverse outcomes. In the U.S. general population, the estimated background risk of major birth defects and miscarriage in clinically recognized pregnancies is 2 to 4% and 15 to 20%, respectively.

Clinical Considerations

Fetal/Neonatal Adverse Reactions

Use of opioid analgesics for an extended period of time during pregnancy for medical or nonmedical purposes can result in physical dependence in the neonate and neonatal opioid withdrawal syndrome shortly after birth. Neonatal opioid withdrawal syndrome presents as irritability, hyperactivity and abnormal sleep pattern, high pitched cry, tremor, vomiting, diarrhea, and failure to gain weight. The onset, duration, and severity of neonatal withdrawal syndrome vary based on the specific opioid used, duration of use, timing and amount of last maternal use, and rate of elimination of the drug by the newborn. Observe newborns for signs of neonatal opioid withdrawal syndrome and manage accordingly [see Warnings and Precautions (5.4)].

Labor or Delivery

Opioids cross the placenta and may produce respiratory depression and psycho-physiologic effects in neonates. An opioid overdose reversal agent, such as naloxone or nalmefene, must be available for reversal of opioid induced respiratory depression in the neonate. Morphine Sulfate Injection is not recommended for use in women during and immediately prior to labor, when use of shorter-acting analgesics or other analgesic techniques are more appropriate. Opioid analgesics, including Morphine Sulfate Injection, can prolong labor through actions that temporarily reduce the strength, duration, and frequency of uterine contractions. However, this effect is not consistent and may be offset by an increased rate of cervical dilatation, which tends to shorten labor. Monitor neonates exposed to opioid analgesics during labor for signs of excess sedation and respiratory depression.

Data

Human Data

The results from a population-based prospective cohort, including 70 women exposed to morphine during the first trimester of pregnancy and 448 women exposed to morphine at any time during pregnancy, indicate no increased risk for congenital malformations. However, these studies cannot definitely establish the absence of any risk because of methodological limitations, including small sample size and non-randomized study design.

Animal Data

Formal reproductive and developmental toxicology studies for morphine have not been conducted. Exposure margins for the following published study reports are based on human daily dose of 60 mg morphine using a body surface area comparison (HDD).

Neural tube defects (exencephaly and cranioschisis) were noted following subcutaneous administration of morphine sulfate (35–322 mg/kg) on Gestation Day 8 to pregnant hamsters (4.7 to 43.5 times the HDD). A no adverse effect level was not defined in this study and the findings cannot be clearly attributed to maternal toxicity. Neural tube defects (exencephaly), axial skeletal fusions, and cryptorchidism were reported following a single subcutaneous injection of morphine sulfate to pregnant mice (100–500 mg/kg) on Gestation Day 8 or 9 at 200 mg/kg or greater (16 times the HDD) and fetal resorption at 400 mg/kg or higher (32 times the HDD). No adverse effects were noted following 100 mg/kg morphine in this model (8 times the HDD). In one study, following continuous subcutaneous infusion of doses greater than or equal to 2.72 mg/kg to mice (0.2 times the HDD), exencephaly, hydronephrosis, intestinal hemorrhage, split supraoccipital, malformed sternebrae, and malformed xiphoid were noted. The effects were reduced with increasing daily dose; possibly due to rapid induction of tolerance under these infusion conditions. The clinical significance of this report is not clear.

Decreased fetal weights were observed in pregnant rats treated with 20 mg/kg/day morphine sulfate (3.2 times the HDD) from Gestation Day 7 to 9. There was no evidence of malformations despite maternal toxicity (10% mortality). In a second rat study, decreased fetal weight and increased incidences of growth retardation were noted at 35 mg/kg/day (5.7 times the HDD) and there was a reduced number of fetuses at 70 mg/kg/day (11.4 times the HDD) when pregnant rats were treated with 10, 35, or 70 mg/kg/day morphine sulfate via continuous infusion from Gestation Day 5 to 20. There was no evidence of fetal malformations or maternal toxicity.

An increased incidence of abortion was noted in a study in which pregnant rabbits were treated with 2.5 (0.8 times the HDD) to 10 mg/kg morphine sulfate via subcutaneous injection from Gestation Day 6 to 10. In a second study, decreased fetal body weights were reported following treatment of pregnant rabbits with increasing doses of morphine (10–50 mg/kg/day) during the pre-mating period and 50 mg/kg/day (16 times the HDD) throughout the gestation period. No overt malformations were reported in either publication; although only limited endpoints were evaluated.

In published studies in rats, exposure to morphine during gestation and/or lactation periods is associated with: decreased pup viability at 12.5 mg/kg/day or greater (2 times the HDD); decreased pup body weights at 15 mg/kg/day or greater (2.4 times the HDD); decreased litter size, decreased absolute brain and cerebellar weights, cyanosis, and hypothermia at 20 mg/kg/day (3.2 times the HDD); alteration of behavioral responses (play, social-interaction) at 1 mg/kg/day or greater (0.2 times the HDD); alteration of maternal behaviors (e.g., decreased nursing and pup retrievals) in mice at 1 mg/kg or higher (0.08 times the HDD) and rats at 1.5 mg/kg/day or higher (0.2 times the HDD); and a host of behavioral abnormalities in the offspring of rats, including altered responsiveness to opioids at 4 mg/kg/day (0.7 times the HDD) or greater.

Fetal and/or postnatal exposure to morphine in mice and rats has been shown to result in morphological changes in fetal and neonatal brain and neuronal cell loss, alteration of a number of neurotransmitter and neuromodulator systems, including opioid and non-opioid systems, and impairment in various learning and memory tests that appear to persist into adulthood. These studies were conducted with morphine treatment usually in the range of 4 to 20 mg/kg/day (0.7 to 3.2 times the HDD).

Additionally, delayed sexual maturation and decreased sexual behaviors in female offspring at 20 mg/kg/day (3.2 times the HDD), and decreased plasma and testicular levels of luteinizing hormone and testosterone, decreased testes weights, seminiferous tubule shrinkage, germinal cell aplasia, and decreased spermatogenesis in male offspring were also observed at 20 mg/kg/day (3.2 times the HDD). Decreased litter size and viability were observed in the offspring of male rats that were intraperitoneally administered morphine sulfate for 1 day prior to mating at 25 mg/kg/day (4.1 times the HDD) and mated to untreated females. Decreased viability and body weight and/or movement deficits in both first and second generation offspring were reported when male mice were treated for 5 days with escalating doses of 120 to 240 mg/kg/day morphine sulfate (9.7 to 19.5 times the HDD) or when female mice treated with escalating doses of 60 to 240 mg/kg/day (4.9 to 19.5 times the HDD) followed by a 5-day treatment-free recovery period prior to mating. Similar multigenerational findings were also seen in female rats pre-gestationally treated with escalating doses of 10 to 22 mg/kg/day morphine (1.6 to 3.6 times the HDD).

8.2 Lactation

Risk Summary

Morphine is present in breast milk. Published lactation studies report variable concentrations of morphine in breast milk with administration of immediate-release morphine to nursing mothers in the early postpartum period with a milk-to-plasma morphine AUC ratio of 2.5:1 measured in one lactation study. However, there is insufficient information to determine the effects of morphine on the breastfed infant and the effects of morphine on milk production. Lactation studies have not been conducted with Morphine Sulfate Injection, and no information is available on the effects of the drug on the breastfed infant or the effects of the drug on milk production.

The developmental and health benefits of breastfeeding should be considered along with the mother's clinical need for Morphine Sulfate Injection, and any potential adverse effects on the breastfed infant from Morphine Sulfate Injection, or from the underlying maternal condition.

Clinical Considerations

Monitor infants exposed to Morphine Sulfate Injection through breast milk for excess sedation and respiratory depression. Withdrawal symptoms can occur in breastfed infants when maternal administration of morphine is stopped, or when breastfeeding is stopped.

8.3 Females and Males of Reproductive Potential

Infertility

Use of opioids for an extended period of time may cause reduced fertility in females and males of reproductive potential. It is not known whether these effects on fertility are reversible [see Clinical Pharmacology (12.2)].

In published animal studies, morphine administration adversely effected fertility and reproductive endpoints in male rats and prolonged estrus cycle in female rats [see Nonclinical Toxicology (13)].

8.4 Pediatric Use

The safety and effectiveness of morphine continuous intravenous infusion in pain management have been established in pediatric patients for all age groups.

Use of morphine continuous intravenous infusion for pain management in pediatric patients is supported by evidence from randomized controlled studies in pediatric patients.

Monitor cardiorespiratory function in patients less than 3 months of age. Adjust the infusion rate based on clinical signs of inadequate pain relief and/or increased somnolence [see Dosage and Administration (2.2)].

For premature infants and former premature infants with chronic lung disease and up to 5 to 6 months of age, careful monitoring for depressed hypoxic drive is required following opioid administration [see Dosage and Administration (2.2)].

8.5 Geriatric Use

The pharmacodynamic effects of morphine in the elderly are more variable than in the younger population. Older patients will vary widely in the effective initial dose, rate of development of tolerance and the frequency and magnitude of associated adverse effects as the dose is increased. Initial elderly patients (aged 65 years or older) may have increased sensitivity to morphine. In general, use caution when selecting a dosage for an elderly patient, usually starting at the low end of the dosing range, reflecting the greater frequency of decreased hepatic, renal, or cardiac function and of concomitant disease or other drug therapy.

Respiratory depression is the chief risk for elderly patients treated with opioids, and has occurred after large initial doses were administered to patients who were not opioid-tolerant or when opioids were co-administered with other agents that depress respiration. Titrate the dosage of Morphine Sulfate Injection slowly in geriatric patients and monitor closely for signs of central nervous system and respiratory depression [see Warnings and Precautions (5.7)].

Morphine is known to be substantially excreted by the kidney, and the risk of adverse reactions to this drug may be greater in patients with impaired renal function. Because elderly patients are more likely to have decreased renal function, care should be taken in dose selection, and it may be useful to monitor renal function.

8.6 Hepatic Impairment

Morphine pharmacokinetics have been reported to be significantly altered in patients with cirrhosis. Start these patients with a lower than normal dosage of Morphine Sulfate Injection and titrate slowly while monitoring for signs of respiratory depression, sedation, and hypotension [see Clinical Pharmacology (12.3)].

8.7 Renal Impairment

Morphine pharmacokinetics are altered in patients with renal failure. Start these patients with a lower than normal dosage of Morphine Sulfate Injection and titrate slowly while monitoring for signs of respiratory depression, sedation, and hypotension [see Clinical Pharmacology (12.3)].

9 DRUG ABUSE AND DEPENDENCE

9.1 Controlled Substance

Morphine Sulfate Injection contains morphine, a Schedule II controlled substance.

9.2 Abuse

Morphine Sulfate Injection contains morphine, a substance with high potential for misuse and abuse, which can lead to the development of ‎substance use disorder, including addiction [see Warnings and Precautions (5.1)].

Misuse is the intentional use, for therapeutic purposes, of a drug by an ‎individual in a way other than ‎prescribed by a healthcare provider or for ‎whom it was not prescribed.‎

Abuse is the intentional, non-therapeutic use of a drug, even once, for its ‎desirable psychological or physiological effects.

Drug addiction is a cluster of behavioral, cognitive, and physiological phenomena that may include a strong desire to take the drug, difficulties in controlling drug use (e.g, continuing drug use despite harmful consequences, giving a higher priority to drug use than to other activities and obligations), and possible tolerance or physical dependence.

Misuse and abuse of Morphine Sulfate Injection increases risk of overdose, which may lead to central nervous system and respiratory depression, hypotension, seizures, and death. The risk is increased with concurrent abuse of Morphine Sulfate Injection with alcohol and/or other CNS depressants. Abuse of and addiction to opioids in some individuals may not be accompanied by concurrent tolerance and symptoms of physical dependence. In addition, abuse of opioids can occur in the absence of addiction.

All patients treated with opioids require careful and frequent reevaluation for signs of misuse, abuse and addiction, because use of opioid analgesic products carries the risk of addiction even under appropriate medical use. Patients at high risk of Morphine Sulfate Injection abuse include those with ‎a history of prolonged use ‎of any opioid, including products containing morphine, those with a ‎history of drug or alcohol abuse, or those who use ‎Morphine Sulfate ‎Injection in combination with other abused drugs.‎

“Drug-seeking” behavior is very common in persons with substance use disorders. Drug-seeking tactics include emergency calls or visits near the end of office hours, refusal to undergo appropriate examination, testing or referral, repeated “loss” of prescriptions, tampering with prescriptions, and reluctance to provide prior medical records or contact information for other treating healthcare provider(s). “Doctor shopping” (visiting multiple prescribers to obtain additional prescriptions) is common among people who abuse drugs and people with substance use disorder. Preoccupation with achieving adequate pain relief can be appropriate behavior in a patient with inadequate pain control.

Morphine Sulfate Injection, like other opioids, can be diverted for nonmedical use into illicit channels of distribution. Careful record-keeping of prescribing information, including quantity, frequency, and renewal requests, as required by state and federal law, is strongly advised.

Proper assessment of the patient, proper prescribing practices, periodic reevaluation of therapy, and proper dispensing and storage are appropriate measures that help to limit abuse of opioid drugs.

Risks Specific to Abuse of Morphine Sulfate Injection

Abuse of Morphine Sulfate Injection poses a risk of overdose and death. The risk is increased with concurrent use of Morphine Sulfate Injection with alcohol and/or other CNS depressants.

Parenteral drug abuse is commonly associated with transmission of ‎infectious diseases such as hepatitis ‎and HIV.‎

9.3 Dependence

Both tolerance and physical dependence can develop during use of opioid therapy.

Tolerance is a physiological state characterized by a reduced response to ‎a drug after repeated administration (i.e., a ‎higher dose of a drug is ‎required to produce the same effect that was once obtained at a lower ‎dose).‎

Physical dependence is a state that develops as a result of a physiological ‎adaptation in response to repeated drug use, ‎manifested by withdrawal ‎signs and symptoms after abrupt discontinuation or a significant dose ‎‎reduction of a drug.‎

Withdrawal may be precipitated through the administration of drugs with opioid antagonist activity (e.g., naloxone, nalmefene), mixed agonist/antagonist analgesics (e.g., pentazocine, butorphanol, nalbuphine), or partial agonists (e.g., buprenorphine). Physical dependence may not occur to a clinically significant degree until after several days to weeks of continued use.

Morphine Sulfate Injection should not be rapidly reduced or abruptly discontinued in a physically-dependent patient [see Dosage and Administration (2.4)]. If Morphine Sulfate Injection is rapidly reduced or abruptly discontinued in a physically‑dependent patient, a withdrawal syndrome may occur‎, typically ‎characterized by restlessness, lacrimation, rhinorrhea, perspiration, chills, myalgia, and mydriasis. Other signs and symptoms also may develop, including irritability, anxiety, backache, joint pain, weakness, abdominal cramps, insomnia, nausea, anorexia, vomiting, diarrhea, or increased blood pressure, respiratory rate, or heart rate.

Infants born to mothers physically-dependent on opioids will also be physically-dependent and may exhibit respiratory difficulties and withdrawal signs [see Use in Specific Populations (8.1)].

10 OVERDOSAGE

Clinical Presentation

Acute overdose with morphine sulfate can be manifested by respiratory depression, somnolence progressing to stupor or coma, skeletal muscle flaccidity, cold and clammy skin, constricted pupils, and, in some cases, pulmonary edema, bradycardia, hypotension, hypoglycemia, partial or complete airway obstruction, atypical snoring, and death. Marked mydriasis rather than miosis may be seen with hypoxia in overdose situations [see Clinical Pharmacology (12.2)]. Toxic leukoencephalopathy has been reported after opioid overdose and can present hours, days, or weeks after apparent recovery from the initial intoxication.

Treatment of Overdose

In case of overdose, priorities are the reestablishment of a patent and protected airway and institution of assisted or controlled ventilation, if needed. Employ supportive measures (including oxygen and vasopressors) in the management of circulatory shock and pulmonary edema as indicated. Cardiac arrest or arrhythmias will require advanced life-support measures.

For clinically significant respiratory or circulatory depression secondary to morphine overdose, administer an opioid overdose reversal agent such as naloxone or nalmefene.

Because the duration of opioid reversal is expected to be less than the duration of action of morphine in Morphine Sulfate Injection, carefully monitor the patient until spontaneous respiration is reliably re-established. If the response to an opioid overdose reversal agent is suboptimal or only brief in nature, administer additional reversal agent as directed by the product's prescribing information.

In an individual physically dependent on opioids, administration of the recommended dosage of the overdose reversal agent will precipitate an acute withdrawal syndrome. The severity of the withdrawal symptoms experienced will depend on the degree of physical dependence and the dose of the reversal agent administered. If a decision is made to treat serious respiratory depression in the physically-dependent patient, administration of the reversal agent should begin with care and by titration with smaller than usual doses of the reversal agent.

11 DESCRIPTION

Morphine, an opioid agonist, is isolated in the form of sulfate salt and pentahydrate, which has the chemical name as 7,8-Didehydro-4,5-epoxy-17-methyl-(5α,6α)-morphinan-3,6-diol sulfate (2:1) (salt), pentahydrate. It has a molecular weight of 758.83 and a chemical formula of (C17H19NO3)2 ∙ H2SO4 ∙ 5H2O, with the following structural formula:

Morphine sulfate USP is an odorless, white crystalline powder with a bitter taste. When exposed to air, it gradually loses water of hydration, and darkens on prolonged exposure to light. It has a solubility of 1 in 21 parts of water and 1 in 1000 parts of alcohol, but is practically insoluble in chloroform or ether. The octanol:water partition coefficient of morphine is 1.42 at physiologic pH and the pKa is 7.9 for the tertiary nitrogen (the majority is ionized at pH 7.4).

Morphine Sulfate Injection, USP is a sterile, nonpyrogenic solution of morphine sulfate, free of antioxidants and preservatives, to be administered by the intravenous route. It is available in 1,000 mg/20 mL (50 mg/mL) and 2,500 mg/50 mL (50 mg/mL) single-dose flip top vials for the preparation of large volume parenteral solutions.

Each milliliter of sterile solution contains 50 mg Morphine Sulfate, USP (Pentahydrate) and the following inactive ingredients: 0.2 mg edetate disodium, 0.8 mg citric acid, sodium chloride to adjust isotonicity, and water for injection. Hydrochloric acid and/or sodium hydroxide may be added to adjust pH. The pH range is 2.5 to 4.0.

12 CLINICAL PHARMACOLOGY

12.1 Mechanism of Action

Morphine is a full opioid agonist and is relatively selective for the mu-opioid receptor, although it can bind to other opioid receptors at higher doses. The principal therapeutic action of morphine is analgesia. Like all full opioid agonists, there is no ceiling effect for analgesia with morphine. Clinically, dosage is titrated to provide adequate analgesia and may be limited by adverse reactions, including respiratory and CNS depression.

The precise mechanism of the analgesic action is unknown. However, specific CNS opioid receptors for endogenous compounds with opioid-like activity have been identified throughout the brain and spinal cord and are thought to play a role in the analgesic effects of this drug.

12.2 Pharmacodynamics

Effects on the Central Nervous System

Morphine sulfate produces respiratory depression by direct action on brain stem respiratory centers. The respiratory depression involves a reduction in the responsiveness of the brain stem respiratory centers to both increases in carbon dioxide tension and electrical stimulation.

Morphine causes miosis, even in total darkness. Pinpoint pupils are a sign of opioid overdose but are not pathognomonic (e.g., pontine lesions of hemorrhagic or ischemic origins may produce similar findings). Marked mydriasis rather than miosis may be seen due to hypoxia in overdose situations.

Effects on the Gastrointestinal Tract and Other Smooth Muscle

Morphine causes a reduction in motility associated with an increase in smooth muscle tone in the antrum of the stomach duodenum. Digestion of food in the small intestine is delayed and propulsive contractions are decreased. Propulsive peristaltic waves in the colon are decreased, while tone may be increased to the point of spasm, resulting in constipation. Other opioid-induced effects may include a reduction in biliary and pancreatic secretions, spasm of sphincter of Oddi, transient elevations in serum amylase, and opioid‑induced esophageal dysfunction (OIED).

Effects of the Cardiovascular System

Morphine produces peripheral vasodilation which may result in orthostatic hypotension or syncope. Manifestations of histamine release and/or peripheral vasodilation may include pruritus, flushing, red eyes, sweating, and/or orthostatic hypotension.

Effects on the Endocrine System

Opioids inhibit the secretion of adrenocorticotropic hormone (ACTH), cortisol, and luteinizing hormones (LH) in humans. They also stimulate prolactin, growth hormone (GH) secretion, and pancreatic secretion of insulin and glucagon.

Use of opioids for an extended period of time may influence the hypothalamic-pituitary-gonadal axis, leading to androgen deficiency that may manifest as low libido, impotence, erectile dysfunction, amenorrhea, or infertility. The causal role of opioids in the clinical syndrome of hypogonadism is unknown because the various medical, physical, lifestyle, and psychological stressors that may influence gonadal hormone levels have not been adequately controlled for in studies conducted to date [see Adverse Reactions (6)].

Effects on the Immune System

Opioids have been shown to have a variety of effects on components of the immune system in in vitro and animal models. The clinical significance of these findings is unknown. Overall, the effects of opioids appear to be modestly immunosuppressive.

Concentration–Efficacy Relationships

The minimum effective analgesic concentration will vary widely among patients, especially among patients who have been previously treated with opioid agonists. The minimum effective analgesic concentration of morphine for any individual patient may increase over time due to an increase in pain, the development of a new pain syndrome, and/or the development of analgesic tolerance [see Dosage and Administration (2.1, 2.2)].

Concentration–Adverse Reaction Relationships

There is a relationship between increasing morphine sulfate plasma concentration and increasing frequency of dose-related opioid adverse reactions such as nausea, vomiting, CNS effects, and respiratory depression. In opioid-tolerant patients, the situation may be altered by the development of tolerance to opioid-related adverse reactions [see Dosage and Administration (2.1, 2.2, 2.4)].

12.3 Pharmacokinetics

Distribution

Morphine has an apparent volume of distribution ranging from 1.0 to 4.7 L/kg after parenteral administration. Protein binding is low, about 36%, and muscle tissue binding is reported as 54%. A blood-brain barrier exists, and when morphine is introduced outside of the CNS, plasma concentrations of morphine remain higher than the corresponding CSF morphine levels.

Elimination

Morphine has a total plasma clearance which ranges from 0.9 to 1.2 L/kg/h in postoperative patients, but shows considerable inter individual variation.

Metabolism

The major pathway of clearance is hepatic glucuronidation to morphine-3-glucuronide, which is pharmacologically inactive.

Excretion

The major excretion path of the conjugate is through the kidneys, with about 10% in the feces. Morphine is also eliminated by the kidneys, 2 to 12% being excreted unchanged in the urine. Terminal half-life is commonly reported to vary from 1.5 to 4.5 hours, although the longer half-lives were obtained when morphine levels were monitored over protracted periods with very sensitive radioimmunoassay methods. The accepted elimination half-life in normal subjects is 1.5 to 2 hours.

Specific population

Sex

While evidence of greater postoperative Morphine Sulfate Injection consumption in men compared to women is present in the literature, clinically significant differences in analgesic outcomes and pharmacokinetic parameters have not been consistently demonstrated. Some studies have shown an increased sensitivity to the adverse effects of Morphine Sulfate Injection, including respiratory depression, in women compared to men.

Hepatic Impairment

Morphine pharmacokinetics are altered in patients with cirrhosis. Clearance was found to decrease with a corresponding increase in half-life. The M3G and M6G to morphine AUC ratios also decreased in these subjects, indicating diminished metabolic activity. Adequate studies of the pharmacokinetics of morphine in patients with severe hepatic impairment have not been conducted.

Renal Impairment

Morphine pharmacokinetics are altered in patients with renal failure. The AUC is increased and clearance is decreased and the metabolites, M3G and M6G, may accumulate to much higher plasma levels in patients with renal failure as compared to patients with normal renal function. Adequate studies of the pharmacokinetics of morphine in patients with severe renal impairment have not been conducted.

13 NONCLINICAL TOXICOLOGY

13.1 Carcinogenesis, Mutagenesis, Impairment of Fertility

Carcinogenesis

Long-term studies in animals to evaluate the carcinogenic potential of morphine have not been conducted.

Mutagenesis

No formal studies to assess the mutagenic potential of morphine have been conducted. In the published literature, morphine was found to be mutagenic in vitro increasing DNA fragmentation in human T-cells. Morphine was also reported to be mutagenic in the in vivo mouse micronucleus assay and positive for the induction of chromosomal aberrations in mouse spermatids and murine lymphocytes. Mechanistic studies suggest that the in vivo clastogenic effects reported with morphine in mice may be related to increases in glucocorticoid levels produced by morphine in these species. In contrast to the above positive findings, in vitro studies in the literature have also shown that morphine did not induce chromosomal aberrations in human leukocytes or translocations or lethal mutations in Drosophila.

Impairment of Fertility

No formal nonclinical studies to assess the potential of morphine to impair fertility have been conducted.

Several nonclinical studies from the literature have demonstrated adverse effects on male fertility in the rat from exposure to morphine. One study in which male rats were administered morphine sulfate subcutaneously prior to mating (up to 30 mg/kg twice daily) and during mating (20 mg/kg twice daily) with untreated females, a number of adverse reproductive effects including reduction in total pregnancies and higher incidence of pseudopregnancies at 20 mg/kg/day (3.2 times the HDD) were reported.

Studies from the literature have also reported changes in hormonal levels in male rats (i.e., testosterone, luteinizing hormone) following treatment with morphine at 10 mg/kg/day or greater (1.6 times the HDD).

Female rats that were administered morphine sulfate intraperitoneally prior to mating exhibited prolonged estrous cycles at 10 mg/kg/day (1.6 times the HDD).

Exposure of adolescent male rats to morphine has been associated with delayed sexual maturation and following mating to untreated females, smaller litters, increased pup mortality, and/or changes in reproductive endocrine status in adult male offspring have been reported (estimated 5 times the plasma levels at the HDD).

16 HOW SUPPLIED/STORAGE AND HANDLING

Morphine Sulfate Injection, USP is a clear and colorless to pale yellow solution supplied as a sterile solution in glass, single-dose flip top vials for the preparation of large volume parenteral solutions.

Unit of Sale | Concentration
NDC 0409-1896-20 Carton containing 1 Single-Dose Flip Top Vial | 1,000 mg/20 mL (50 mg/mL)
NDC 0409-2022-01 Carton containing 1 Single-Dose Flip Top Vial | 2,500 mg/50 mL (50 mg/mL)

STORAGE AND HANDLING

Store at 20°C to 25°C (68°F to 77°F) [See USP Controlled Room Temperature] until ready to use. PROTECT FROM LIGHT. DO NOT FREEZE. Contains no preservative or antioxidant. DISCARD ANY UNUSED PORTION. DO NOT HEAT-STERILIZE.

17 PATIENT COUNSELING INFORMATION

Addiction, Abuse, and Misuse

Inform patients that the use of Morphine Sulfate Injection, even when taken as recommended, can result in addiction, abuse, and misuse, which can lead to overdose and death [see Warnings and Precautions (5.1)]. Instruct patients not to share Morphine Sulfate Injection with others and to take steps to protect Morphine Sulfate Injection from theft or misuse.

Life-Threatening Respiratory Depression

Inform patients of the risk of life-threatening respiratory depression, including information that the risk is greatest when starting Morphine Sulfate Injection or when the dosage is increased, and that it can occur even at recommended dosages [see Warnings and Precautions (5.2)].

Hyperalgesia and Allodynia

Advise ‎patients to inform their healthcare provider if they ‎experience symptoms of hyperalgesia, including worsening ‎pain, increased ‎sensitivity to pain, or new pain [see Warnings and Precautions (5.6), ‎Adverse Reactions (6)].‎

Serotonin Syndrome

Inform patients that opioids can cause a rare but potentially life-threatening condition called serotonin syndrome resulting from concomitant administration of serotonergic drugs. Warn patients of the symptoms of serotonin syndrome and to seek medical attention right away if symptoms develop after discharge from the hospital. Instruct patients to inform their physicians if they are taking, or plan to take serotonergic medications [see Drug Interactions (7)].

Constipation

Advise patients of the potential for severe constipation, including management instructions and when to seek medical attention [see Adverse Reactions (6)].

For Medical Information about Morphine Sulfate Injection, please visit www.pfizermedinfo.com or ‎call 1-800-438-1985.‎

Distributed by Hospira, Inc., Lake Forest, IL 60045 USA

LAB-1306-4.0

PRINCIPAL DISPLAY PANEL - 20 mL Vial Label

20 mL Single-Dose Vial
NDC 0409-1896-20

Rx only

Morphine Sulfate CII
Injection, USP

1,000 mg/20 mL
(50 mg/mL)

FOR INTRAVENOUS USE ONLY
AFTER DILUTION
Not for epidural or intrathecal use
CAUTION: NOT FOR DIRECT INJECTION

PRINCIPAL DISPLAY PANEL - 20 mL Vial Carton

20 mL Single-Dose Vial
NDC 0409-1896-20

Rx only

CII

Morphine Sulfate
Injection, USP

1,000 mg/20 mL
(50 mg/mL)

FOR INTRAVENOUS USE ONLY AFTER
DILUTION
Not for epidural or intrathecal use

CAUTION: NOT FOR DIRECT INJECTION

Hospira

PRINCIPAL DISPLAY PANEL - 50 mL Vial Label

50 mL Single-Dose Vial
Rx only

Morphine Sulfate
Injection, USP
CII

2,500 mg/50 mL
(50 mg/mL)

FOR INTRAVENOUS USE ONLY AFTER DILUTION
Not for epidural or intrathecal use
CAUTION: NOT FOR DIRECT INJECTION

Dist. by Hospira, Inc., Lake Forest, IL 60045 USA

Hospira

PRINCIPAL DISPLAY PANEL - 50 mL Vial Carton

50 mL Single-Dose Vial
NDC 0409-2022-01

Rx only

CII

Morphine Sulfate
Injection, USP

2,500 mg/50 mL
(50 mg/mL)

FOR INTRAVENOUS USE ONLY AFTER
DILUTION
Not for epidural or intrathecal use

CAUTION: NOT FOR DIRECT
INJECTION

Hospira